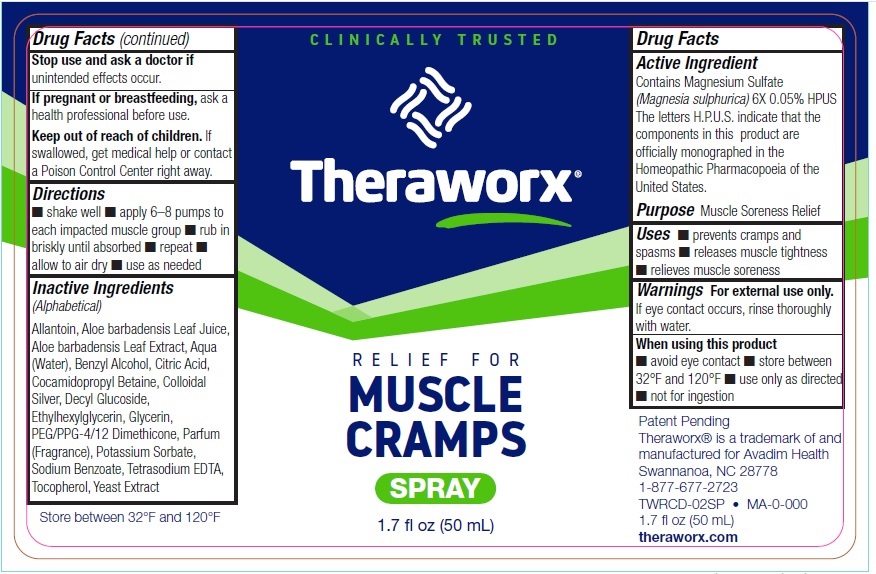 DRUG LABEL: Theraworx Relief for Muscle Cramps
NDC: 61594-026 | Form: SPRAY
Manufacturer: AVADIM HOLDINGS, INC.
Category: homeopathic | Type: HUMAN OTC DRUG LABEL
Date: 20231212

ACTIVE INGREDIENTS: MAGNESIUM SULFATE, UNSPECIFIED FORM 6 [hp_X]/1 mL
INACTIVE INGREDIENTS: COCAMIDOPROPYL BETAINE; SILVER; DECYL GLUCOSIDE; ETHYLHEXYLGLYCERIN; GLYCERIN; PEG/PPG-4/12 DIMETHICONE; POTASSIUM SORBATE; SODIUM BENZOATE; EDETATE SODIUM; TOCOPHEROL; YEAST, UNSPECIFIED; ALLANTOIN; ALOE VERA LEAF; WATER; BENZYL ALCOHOL; CITRIC ACID MONOHYDRATE

Theraworx Relief for Muscle Cramps Spray

Active Ingredient

Contains Magnesium Sulfate (Magnesia sulphurica) 6X 0.05% HPUS
The letters H.P.U.S. indicate that the components in this product are officially monographed in the Homeopathic Pharmacopoeia of the United States.

Purpose

Muscle Soreness Relief

Uses

- prevents cramps and spasms
- releases muscle tightness
- relieves muscle soreness

Warnings

For external use only. If eye contact occurs, rinse thoroughly with water.

When using this product

- avoid eye contact
- store between 32°F and 120°F
- use only as directed
- not for ingestion

Stop use and ask a doctor if

unintended effects occur.

If pregnant or breastfeeding,

ask a health professional before use.

Keep out of reach of children.

If swallowed, get medical help or contact a Poison Control Center right away.

Directions

- shake well
- apply 6–8 pumps to each impacted muscle group
- rub in briskly until absorbed
- repeat
- allow to air dry
- use as needed

Inactive Ingredients (Alphabetical)

Allantoin, Aloe barbadensis Leaf Juice, Aloe barbadensis Leaf Extract, Aqua (Water), Benzyl Alcohol, Citric Acid, Cocamidopropyl Betaine, Colloidal Silver, Decyl Glucoside, Ethylhexylglycerin, Glycerin, PEG/PPG-4/12 Dimethicone, Parfum (Fragrance), Potassium Sorbate, Sodium Benzoate, Tetrasodium EDTA, Tocopherol, Yeast Extract

Store between 32°F and 120°F